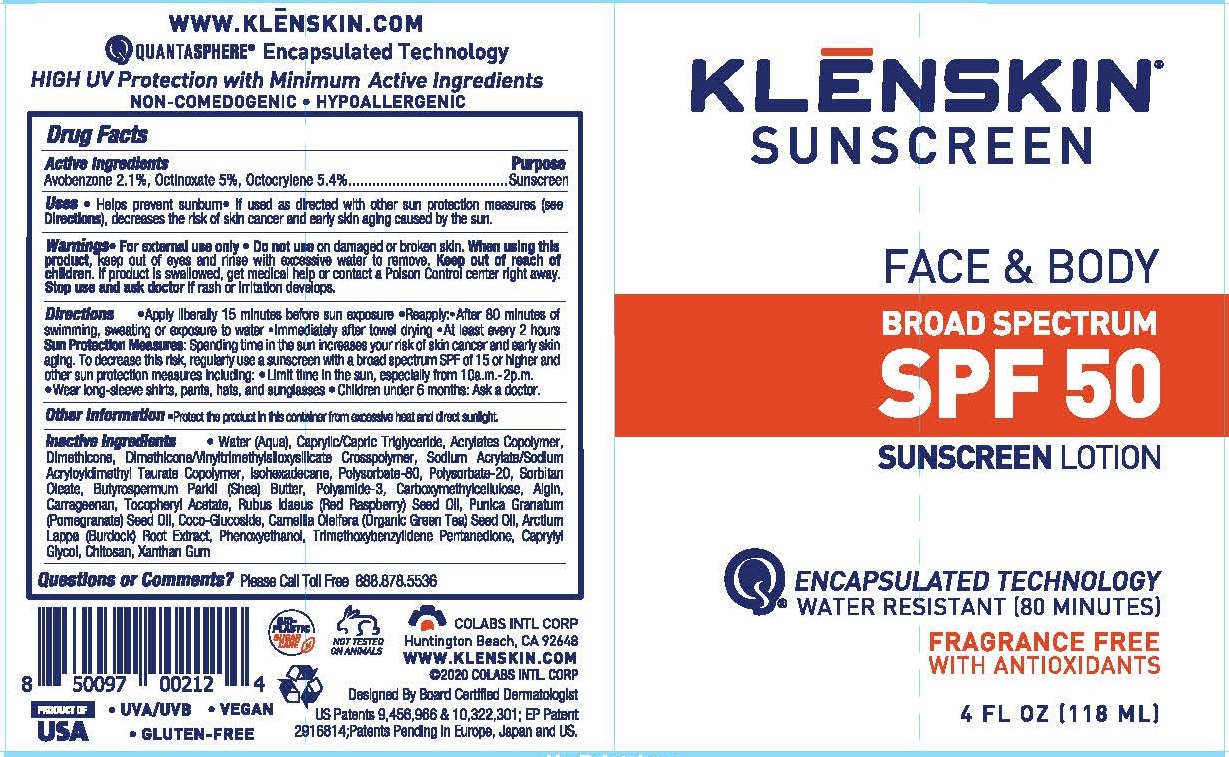 DRUG LABEL: KLENSKIN BROAD SPECTRUM
NDC: 61369-201 | Form: LOTION
Manufacturer: CoLabs Intl. Corp
Category: otc | Type: HUMAN OTC DRUG LABEL
Date: 20240115

ACTIVE INGREDIENTS: AVOBENZONE 2.1 g/100 mL; OCTOCRYLENE 5.4 g/100 mL; OCTINOXATE 5 g/100 mL
INACTIVE INGREDIENTS: WATER; MEDIUM-CHAIN TRIGLYCERIDES; CARBOMER COPOLYMER TYPE A; DIMETHICONE; VINYLDIMETHYL/TRIMETHYLSILOXYSILICATE STEARYL DIMETHICONE CROSSPOLYMER; SODIUM ACRYLATE/SODIUM ACRYLOYLDIMETHYLTAURATE COPOLYMER (4000000 MW); ISOHEXADECANE; POLYSORBATE 80; POLYSORBATE 20; SORBITAN MONOOLEATE; HYDROLYZED WHEAT PROTEIN (ENZYMATIC, 3000 MW); SHEANUT OIL; POLYAMIDE-3 (12000 MW); CARBOXYMETHYLCELLULOSE SODIUM; ETHYLENEDIAMINE; DIISOSTEARYL DIMER DILINOLEATE; HYDROXYETHYL CELLULOSE (100 MPA.S AT 2%); DISTEARYLDIMONIUM CHLORIDE; SODIUM LAURYL GLYCOL CARBOXYLATE; LAURYL GLUCOSIDE; LAURDIMONIUMHYDROXYPROPYL DECYLGLUCOSIDE CHLORIDE; GELLAN GUM (LOW ACYL); SODIUM ALGINATE; CARRAGEENAN; .ALPHA.-TOCOPHEROL ACETATE; RASPBERRY SEED OIL; POMEGRANATE SEED OIL; CAMELLIA SINENSIS SEED OIL; ARCTIUM LAPPA ROOT; PHENOXYETHANOL; CAPRYLYL GLYCOL; TRIMETHOXYBENZYLIDENE PENTANEDIONE

COLABS - KLENSKIN SUNSCREEN - FACE & BODY SPF 50 SUNSCREEN LOTION (61369-201)

ACTIVE INGREDIENTS

AVOBENZONE 2.1%

OCTINOXATE 5%

OCTOCRYLENE 5.4%

PURPOSE

SUNSCREEN

USES

- HELPS PREVENT SUNBURN
- IF USED AS DIRECTED WITH OTHER SUN PROTECTION MEASURES (SEE DIRECTIONS), DECREASES THE RISK OF SKIN CANCER AND EARLY SKIN AGING CAUSED BY THE SUN.

WARNINGS

- FOR EXTERNAL USE ONLY
- DO NOT USE ON DAMAGED OR BROKEN SKIN.
- WHEN USING THIS PRODUCT, KEEP OUT OF EYES AND RINSE WITH EXCESSIVE WATER TO REMOVE.

KEEP OUT OF REACH OF CHILDREN. IF PRODUCT IS SWALLOWED, GET MEDICAL HELP OR CONTACT A POISON CONTROL CENTER RIGHT AWAY.

STOP USE AND ASK A DOCTOR IF RASH OR IRRITATION DEVELOPS.

DIRECTIONS

- SHAKE WELL BEFORE USE
- APPLY LIBERALLY 15 MINUTES BEFORE SUN EXPOSURE
- REAPPLY:
- AFTER 80 MINUTES OF SWIMMING, SWEATING OR EXPOSURE TO WATER
- IMMEDIATELY AFTER TOWEL DRYING
- AT LEAST EVERY 2 HOURS

OTHER SAFETY INFORMATION

SUN PROTECTION MEASURES: SPENDING TIME IN THE SUN INCREASES YOUR RISK OF SKIN CANCER AND EARLY SKIN AGING. TO DECREASE THIS RISK, REGULARLY USE A SUNSCREEN WITH A BROAD SPECTRUM SPF OF 15 OR HIGHER AND OTHER SUN PROTECTION MEASURES INCLUDING:

- LIMIT TIME IN THE SUN, ESPECIALLY FROM 10 A.M. - 2 P.M.
- WEAR LONG-SLEEVED SHIRTS, PANTS, HATS, AND SUNGLASSES
- CHILDREN UNDER 6 MONTHS: ASK A DOCTOR.

OTHER INFORMATION

- PROTECT THE PRODUCT IN THIS CONTAINER FROM EXCESSIVE HEAT AND DIRECT SUNLIGHT.

INACTIVE INGREDIENTS

Water (Aqua), Caprylic/Capric Triglyceride, Acrylates Copolymer, Dimethicone, Vinyldimethyl/Trimethylsiloxysilicate/Dimethicone Crosspolymer, Sodium Acrylate/Sodium Acryloyldimethyl Taurate Copolymer, Isohexadecane, Polysorbate 80, Polysorbate 20, Sorbitan Monooleate, Cocodimonium Hydroxypropyl Hydrolyzed Keratin, Butyrospermum Parkii (Shea) Oil, Polyamide 3, Carboxymethylcellulose Na,
Ethylenediamine/Stearyl Dimer Dilinoleate Copolymer, PG Hydroxyethylcellulose Stearyldimonium Chloride, Sodium Lauryl Glucose Carboxylate, Lauryl Glucoside, Laurdimoniumhydroxypropyl Decylglucosides Chloride, Gellan Gum, Sodium Alginate, Carrageenan, Tocopheryl Acetate, Rubeus Idaeus (Red Raspberry) Oil, Punica Granatum (Pomegranate) Seed Oil, Camellia Oleifera (Organic Green Tea) Seed Oil, Arctium Lappa Root Extract (Burdock Root), Phenoxyethanol, Trimethoxybenzylidene Pentanedione, Caprylyl Glycol

QUESTIONS OR COMMENTS? PLEASE CALL TOLL FREE 888.878.5536